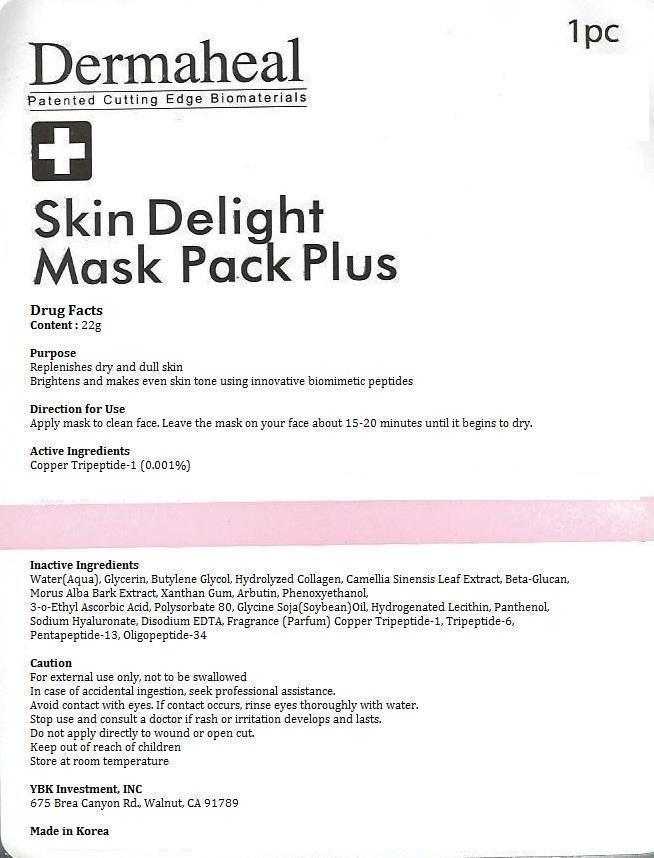 DRUG LABEL: Dermaheal Skin Delight Mask Pack Plus
NDC: 60709-106 | Form: PATCH
Manufacturer: YBK Investment, INC
Category: otc | Type: HUMAN OTC DRUG LABEL
Date: 20131101

ACTIVE INGREDIENTS: PREZATIDE COPPER 0.22 mg/22 g
INACTIVE INGREDIENTS: WATER; GLYCERIN; BUTYLENE GLYCOL; CAMELLIA SINENSIS VAR. ASSAMICA WHOLE; MORUS ALBA BARK; XANTHAN GUM; ARBUTIN; PHENOXYETHANOL; 3-O-ETHYL ASCORBIC ACID; POLYSORBATE 80; SOYBEAN OIL; HYDROGENATED SOYBEAN LECITHIN; PANTHENOL; HYALURONATE SODIUM; EDETATE DISODIUM

Dermaheal Skin Delight Mask Pack Plus

Skin Delight Mask Plack Plus

Purpose

Replenishes dry and dull skin

Brightens and makes even skin tone using innovative biomimetic peptides

Direction for Use

Apply mask to clean face. Leave the mask on your face about 15-20 minutes until it begins to dry.

Caution

For external use only, not to be swallowed

In case of accidental ingestion, seek professional assistance.

Avoid contact with eyes. If contact occurs, rinse eyes thoroughly with water.

Stop use and consult a doctor if rash or irritation develops and lasts.

Do not apply directly to wound or open cut.

Keep out of reach of children

Store at room temperature

Stop use and consult a doctor if rash or irritation develops and lasts.

Purpose

Replenishes dry and dull skin

Brightens and makes even skin tone using innovative biomimetic peptides

Keep out of reach of children

Stop use and consult a doctor if rash or irritation develops and lasts.

INACTIVE INGREDIENT

Water(Aqua), Glycerin, Butylene Glycol, Hydrolyzed Collagen, Camellia Sinensis Leaf Extract, Beta-Glucan, Morus Alba Bark Extract, Xanthan Gum, Arbutin, Phenoxyethanol, 3-o-Ethyl Ascorbic Acid, Polysorbate 80, Glycine Soja(Soybean) Oil, Hydrogenated Lecithin, Panthenol, Sodium Hyaluronate, Disodium EDTA, Fragrance(Parfum), PALMITOYL OLIGOPEPTIDE

WARNINGS

For external use only, not to be swallowed

In case of accidental ingestion, seek professional assistance.

Avoid contact with eyes. If contact occurs, rinse eyes thoroughly with water.

Do not apply directly to wound or open cut.

Store at room temperature

INDICATIONS AND USAGE

Apply mask to clean face. Leave the mask on your face about 15-20 minutes until it begins to dry

DOSAGE AND ADMINISTRATION

One time use only

One mask pack per person

ACTIVE INGREDIENT

Copper Tripeptide-1 (0.001%)